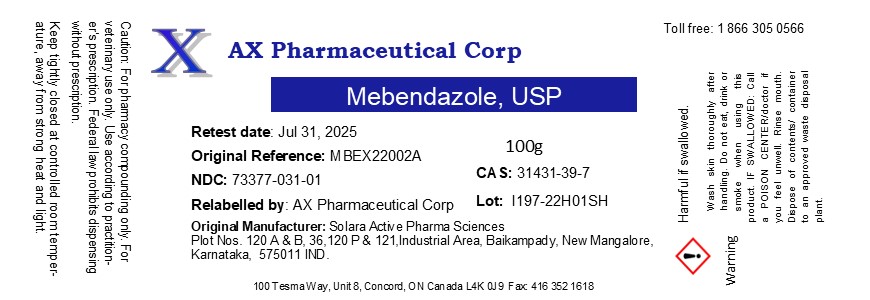 DRUG LABEL: Mebendazole
NDC: 73377-031 | Form: POWDER
Manufacturer: AX Pharmaceutical Corp
Category: other | Type: BULK INGREDIENT - ANIMAL DRUG
Date: 20260119

ACTIVE INGREDIENTS: MEBENDAZOLE 1 g/1 g

Mebendazole